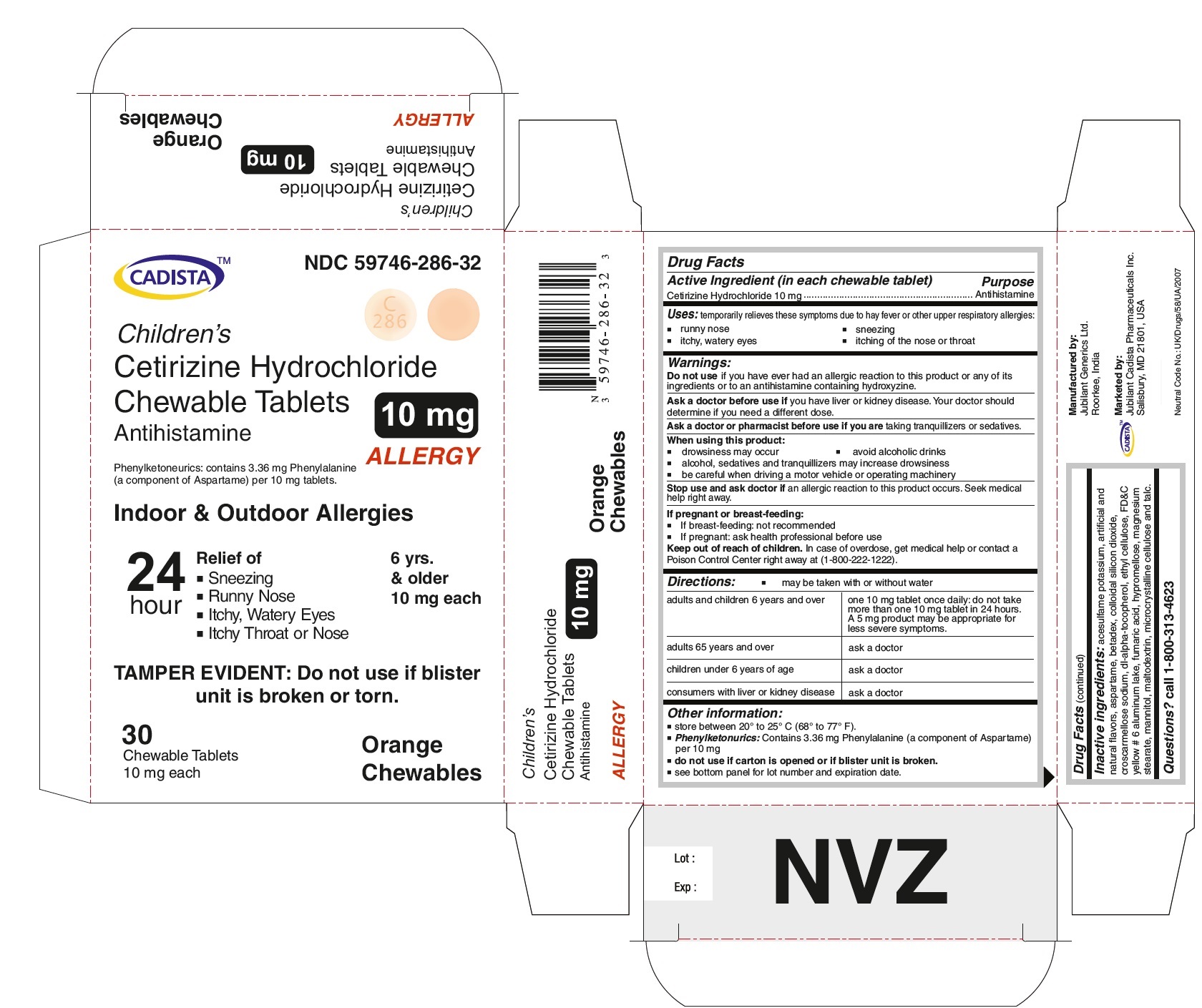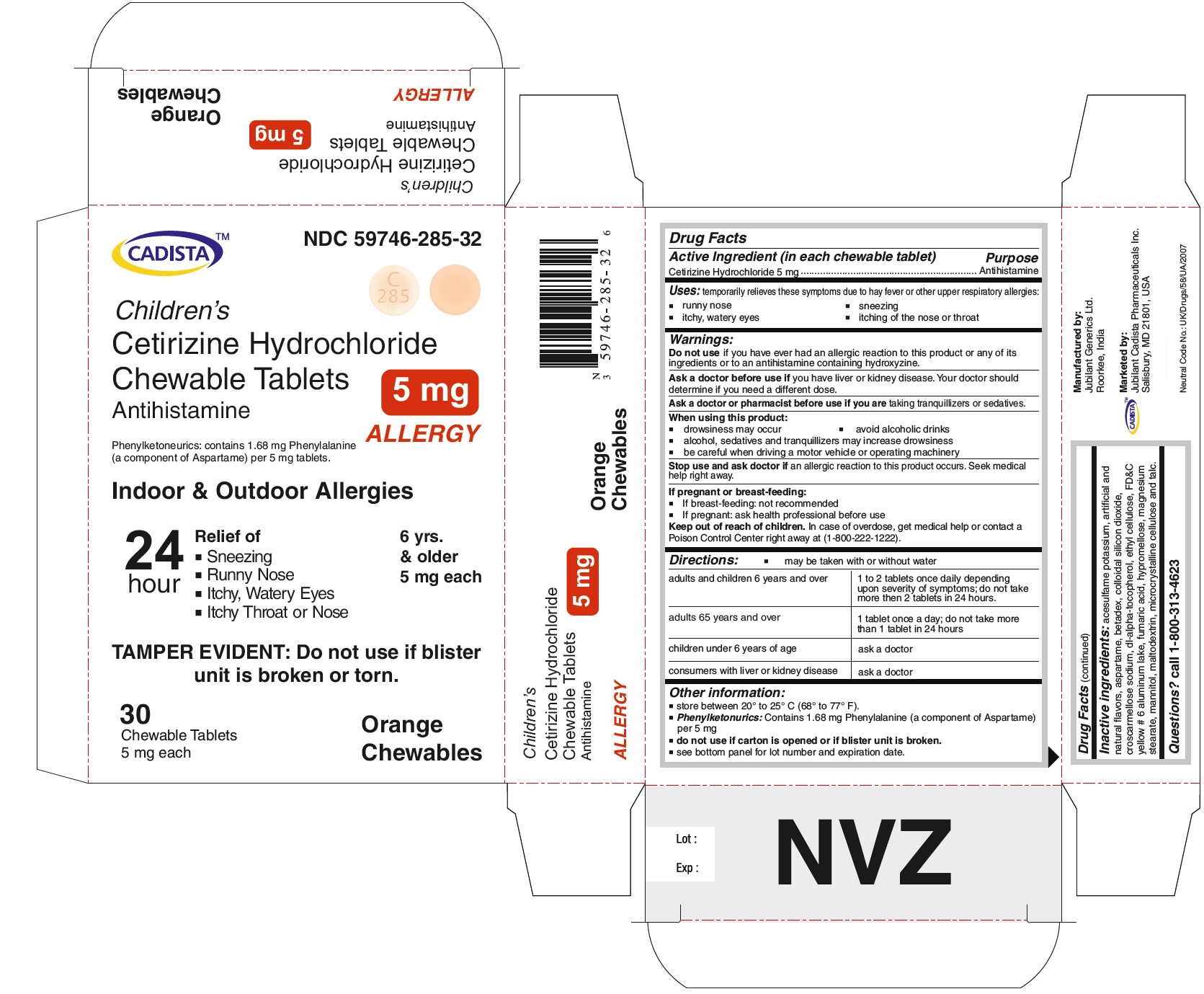 DRUG LABEL: cetirizine hydrochloride 
NDC: 59746-285 | Form: TABLET, CHEWABLE
Manufacturer: Jubilant Cadista Pharmaceuticals Inc.
Category: otc | Type: HUMAN OTC DRUG LABEL
Date: 20191230

ACTIVE INGREDIENTS: Cetirizine Hydrochloride 5 mg/1 1
INACTIVE INGREDIENTS: Acesulfame Potassium; Aspartame; Betadex; Silicon Dioxide; Croscarmellose Sodium; .alpha.-tocopherol, Dl-; Ethylcelluloses; Fd&c Yellow No. 6; Fumaric Acid; Hypromelloses; Magnesium Stearate; Mannitol; Maltodextrin; Cellulose, Microcrystalline; Talc

Childrens's
Cetirizine Hydrochloride Chewable Tablets
Antihistamine
DRUG FACTS

Active Ingredient (in each chewable tablet)

Cetirizine Hydrochloride 5 mg
Cetirizine Hydrochloride 10 mg

Purpose

Antihistamine

Uses:

temporarily relieves these symptoms due to hay fever or other upper respiratory allergies:

- runny nose
- itchy, watery eyes
- sneezing
- itching of the nose or throat

When using this product:

- drowsiness may occur
- avoid alcoholic drinks
- alcohol, sedatives and tranquilizers may increase drowsiness
- be careful when driving a motor vehicle or operating machinery

If pregnant or breast-feeding:

- If breast-feeding: not recommended
- If pregnant: ask a health professional before use

Keep out of reach of children.

In case of overdose, get medical help or contact a Poison Control Center right away at (1-800-222-1222).

Directions:

● may be taken with and without water

For Cetirizine hydrochloride chewable tablets 5 mg

adults and children 6 years and over | 1 to 2 tablets once daily depending upon severity of symptoms; do not take more than 2 tablets in 24 hours.
adults 65 years and over | 1 tablet once a day; do not take more than 1 tablet in 24 hours.
children under 6 years of age | ask a doctor
consumers with liver or kidney disease | ask a doctor

For Cetirizine hydrochloride chewable tablets 10 mg

adults and children 6 years and over | one 10 mg tablet once daily; do not take more than one 10 mg tablet in 24 hours. A 5 mg product may be appropriate for less severe symptoms.
adults 65 years and over | ask a doctor
children under 6 years of age | ask a doctor
consumers with liver or kidney disease | ask a doctor

Other information:

- store between 20º to 25º C (68º to 77º F)
- Phenylketonurics: Contains 1.68 mg Phenylalanine (a component of Aspartame) per 5 mg
- Phenylketonurics: Contains 3.36 mg Phenylalanine (a component of Aspartame) per 10 mg
- do not use if carton is opened or if blister unit is broken.
- see bottom panel for lot number and expiration date.

Inactive ingredients:

acesulfame potassium, artificial and natural flavors, aspartame, betadex, colloidal silicon dioxide, croscarmellose sodium, dl-alpha-tocopherol, ethyl cellulose, FD&C yellow # 6 aluminum lake, fumaric acid, hypromellose, magnesium stearate, mannitol, maltodextrin, microcrystalline cellulose and talc.

Questions? call 1-800-313-4623

Manufactured by:
Jubilant Generics Ltd.
Roorkee-247661, India

Marketed by:
Jubilant Cadista Pharmaceuticals Inc.
Salisbury, MD 21801, USA

Revised : November / 2014

PACKAGE LABEL.PRINCIPAL DISPLAY PANEL

CADISTA NDC 59746-285-32
Children's
Cetirizine Hydrochloride Chewable Tablets 5 mg
Antihistamine
ALLERGY
Phenylketonurics: contains 1.68 mg Phenylalanine (a component of Aspartame) per 5 mg tablets.
Indoor & Outdoor Allergies
24 hour Relief of
● Sneezing
● Running Nose
● Itchy,Watery Eyes
● Itchy Throat or Nose
TAMPER EVIDENT : Do not use if blister unit is broken or torn.
6 yrs. & older
5 mg each
30 Chewable Tablets Orange Chewables
5 mg each

CADISTA NDC 59746-286-32
Children's
Cetirizine Hydrochloride Chewable Tablets 10 mg
Antihistamine
ALLERGY
Phenylketonurics: contains 3.36 mg Phenylalanine (a component of Aspartame) per 10 mg tablets.
Indoor & Outdoor Allergies
24 hour Relief of
● Sneezing
● Running Nose
● Itchy,Watery Eyes
● Itchy Throat or Nose
TAMPER EVIDENT : Do not use if blister unit is broken or torn.
6 yrs. & older
10 mg each
30 Chewable Tablets Orange Chewables
10 mg each